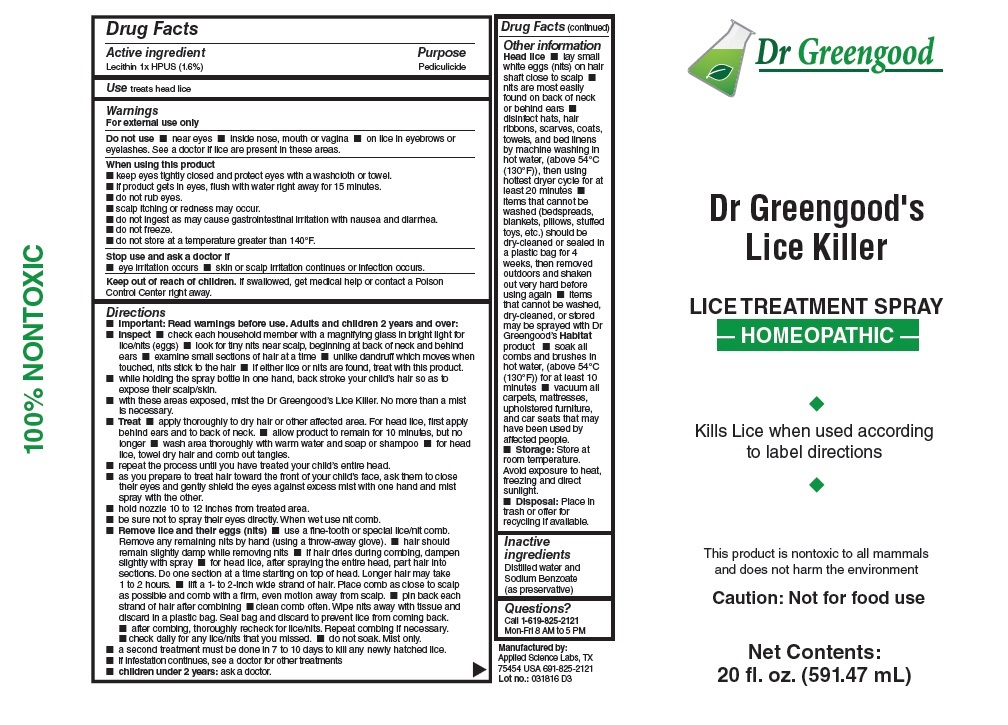 DRUG LABEL: Dr. Greengoods Lice Killer LICE TREATMENT
NDC: 70606-107 | Form: SPRAY
Manufacturer: Applied Science Labs, Inc.
Category: homeopathic | Type: HUMAN OTC DRUG LABEL
Date: 20160414

ACTIVE INGREDIENTS: EGG PHOSPHOLIPIDS 1 [hp_X]/1 mL
INACTIVE INGREDIENTS: SODIUM BENZOATE; WATER

Dr. Greengoods Lice Killer LICE TREATMENT

Active ingredient

Lecithin 1x HPUS (1.6%)

Purpose

Pediculicide

Keep out of reach of children. If swallowed, get medical help or contact a Poison Control Center right away.

INDICATIONS AND USAGE

Use treats head lice

Warnings

For external use only

Do not use • near eyes • inside nose, mouth or vagina • on lice in eyebrows or eyelashes. See a doctor if lice are present in these areas.

When using this product

• keep eyes tightly closed and protect eyes with a washcloth or towel

• if product gets in eyes, flush with water right away for 15 minutes

• do not rub eyes

• scalp itching and redness may occur.

• do not ingest as may cause gastrointestinal irritation with nausea and diarrhea.

• do not freeze

• do not store at a temperature greater than 140° F

Stop use and ask a doctor if

• eye irritation occurs

• skin or scalp irritation continues or infection occurs

Directions

• Important: Read warnings before use. Adults and children 2 years and over:

• Inspect • check each household member with a magnifying glass in bright light for lice/nits (eggs) • look for tiny nits near scalp beginning at back of neck and behind ears • examine small sections of hair at a time • unlike dandruff which moves when touched, nits stick to the hair • if either lice or nits are found, treat with this product.

• while holding the spray bottle in one hand, back stroke your child's hair so as to expose their scalp/skin.

• with these areas exposed, mist the Dr. Greengoods'Lice Killer. No more than a mist is necessary.

• Treat • apply thoroughly to dry hair or other affected area. For head lice, first apply behind ears and to back of neck. • allow product to remain for 10 minutes, but no longer • wash area thoroughly with warm water and soap or shampoo • for head lice, towel dry hair and comb out tangles.

• repeat the process until you have treated your child's entire head.

• as you prepare to treat hair toward the front of your child's face, ask them to close their eyes and gently shield the eyes against excess mist with one hand and mist spray with the other.

• hold nozzle 10 to 12 inches from treated area.

• be sure not to spray their eyes directly. When wet use nit comb.

• Remove lice and their eggs (nits) • use a fine-tooth or special lice/nit comb. Remove any remaining nits by hand (using a throw-away glove). • hair should remain slightly damp while removing nits • if hair dries during combing, dampen slightly with spray • for head lice, after spraying the entire head, part hair into sections. Do one section at a time starting on top of head. Longer hair may take 1 to 2 hours. • lift a 1-to 2-inch wide strand of hair. Place comb as close to scalp as possible and comb with a firm, even motion away from scalp • pin back each strand of hair after combing • clean comb often. Wipe nits away with tissue and discard in a plastic bag. Seal bag and discard to prevent lice from coming back.

• after combing, thoroughly recheck for lice/nits. Repeat combing if necessary

• check daily for any lice/nits that you missed". • do not soak. Mist only.

• a second treatment must be done in 7 to 10 days to kill any newly hatched lice.

• if infestation continues, see a doctor for other treatments

• children under 2 years: ask a doctor

Inactive ingredients

Distilled water and Sodium Benzoate (as preservative)

Other information

Head lice • lay small white eggs (nits) on hair shaft close to scalp • nits are most easily found on back of neck or behind ears • disinfect hats, hair
ribbons, scarves, coats, towels, and bed linens by machine washing in hot water, (above 54°C (130°F)), then using hottest dryer cycle for at least 20 minutes • items that cannot be washed (bedspreads, blankets, pillows, stuffed toys, etc.) should be dry-cleaned or sealed in a plastic bag for 4
weeks, then removed outdoors and shaken out very hard before using again • items that cannot be washed, dry-cleaned, or stored may be sprayed with Dr Greengood’s Habitat product • soak all combs and brushes in hot water, (above 54°C (130°F)) for at least 10 minutes • vacuum all carpets, mattresses, upholstered furniture, and car seats that may have been used by affected people.

• Storage: Store at room temperature. Avoid exposure to heat, freezing and direct sunlight.

• Disposal: Place in trash or offer for recycling if available.

Questions?

Call 1-619-825-2121

Mon-Fri 8 AM to 5 PM

100% NON-TOXIC

Kills Lice when used according to label directions
This product is nontoxic to all mammals and does not harm the environment

Caution: Not for food use

Manufactured by:
Applied Science Labs,
Melissa, TX 75454
USA 619-825-2121